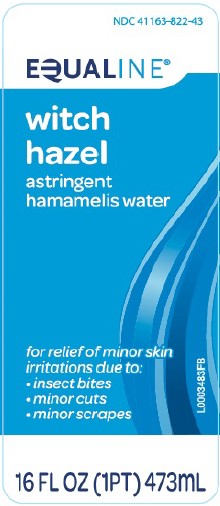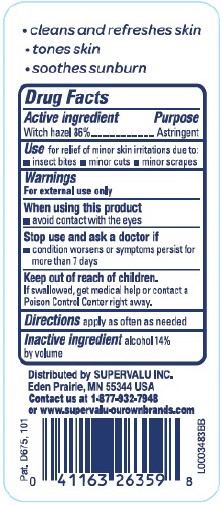 DRUG LABEL: Witch Hazel
NDC: 41163-822 | Form: SOLUTION
Manufacturer: United Natural Foods, Inc. dba UNFI
Category: otc | Type: HUMAN OTC DRUG LABEL
Date: 20260217

ACTIVE INGREDIENTS: WITCH HAZEL 860 mg/1 mL
INACTIVE INGREDIENTS: ALCOHOL

Equaline 822.001/822AA
Witch Hazel

Claims

- cleans and refreshens skin
- tones skin
- soothes sunburn

Active ingredient

Witch hazel 86%

Purpose

Astringent

Use

for relief of minor skin irritations due to:

- insect bites
- minor cuts
- minor scrapes

Warnings

For external use only

When using this product

•avoid contact with the eyes.

Stop use and ask a doctor if

• condition worsens or symptoms persist for more than 7 days

Keep out of reach of children.

If swallowed, get medical help or contact a Poison Control Center right away.

Directions

apply as often as needed

Inactive ingredient

alcohol 14% by volume

Adverse event

Distributed by SUPERVALE INC.

Eden Prairie, MN 55344 USA

Contact us at 1-877-932-7948

or www.supervalu-ourownbrands.com

Pat. D675, 101

Principal display panel

NDC 41163-822-43

EQUALINE®

witch hazel

astringent

hamamelis water

for relief of minor skin irritations due to:

- insects bites
- minor cuts
- minor scrapes

16 FL OZ (1 PT) 473 mL